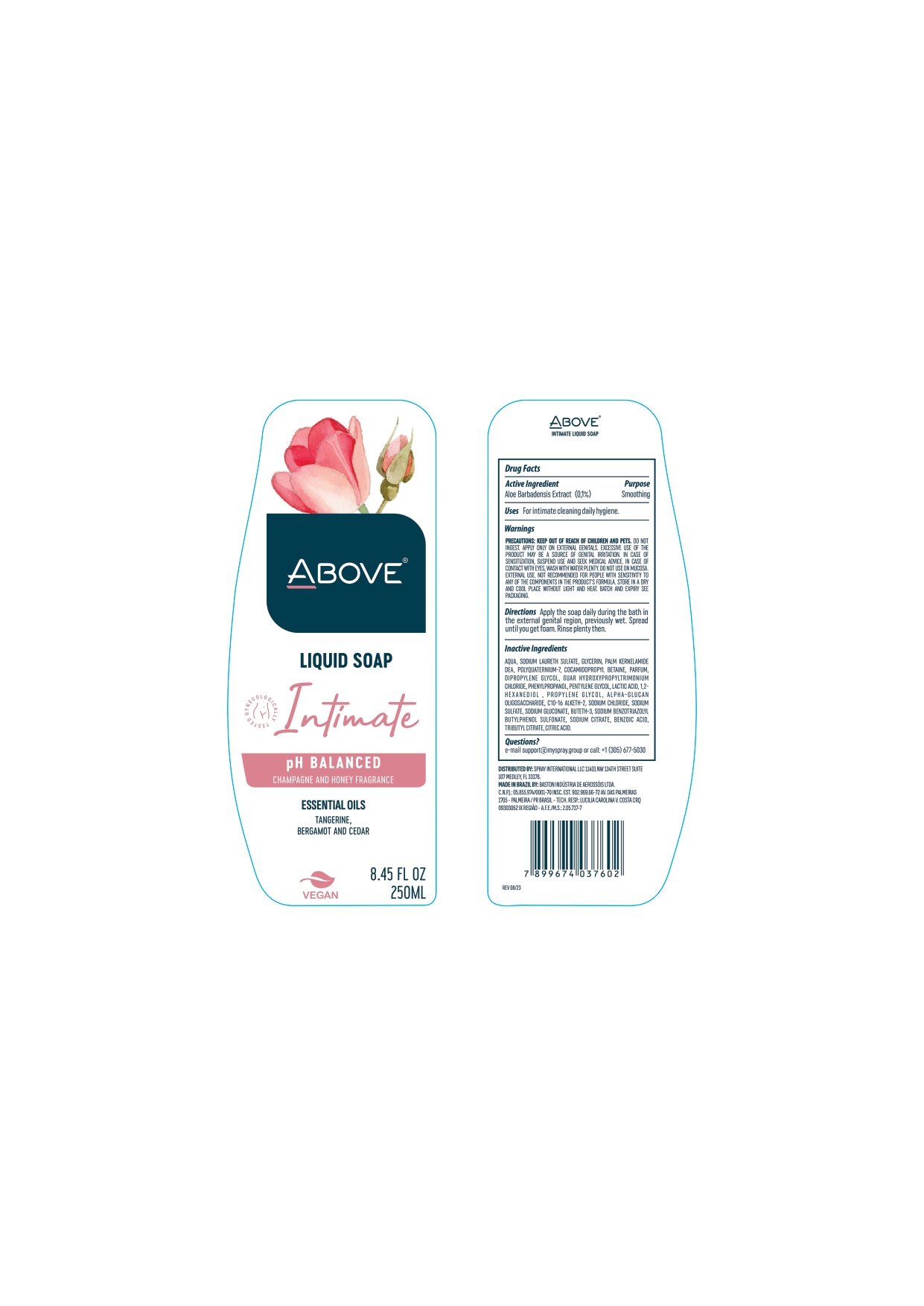 DRUG LABEL: ABOVE INTIMATE  LIQUIDSOAP
NDC: 73306-1161 | Form: LIQUID
Manufacturer: BASTON INDUSTRIA DE AEROSSOIS LTDA
Category: otc | Type: HUMAN OTC DRUG LABEL
Date: 20241226

ACTIVE INGREDIENTS: ALOE 0.01 mg/250 g
INACTIVE INGREDIENTS: SODIUM LAURETH-2 SULFATE

ABOVE INTIMATE LIQUID SOAP

ACTIVE INGREDIENT

ALOE BARBADENSIS EXTRACT (EXTRATO DE ALOE VERA) CONDICIONADOR DA PELE 0.1

INACTIVE INGREDIENT

AQUA (ÁGUA)
SODIUM LAURETH SULFATE (LAURILETERSULFATO DE SÓDIO)
GLYCERIN (GLICEROL)
PALM KERNELAMIDE DEA (PALMISTAMIDA DEA)
POLYQUATERNIUM-7 (POLIQUATÉRNIO-7)
COCAMIDOPROPYL BETAINE (COCOAMIDOPROPIL BETAÍNA)
PARFUM (PERFUME)
DIPROPYLENE GLYCOL (DIPROPILENOGLICOL)
GUAR HYDROXYPROPYLTRIMONIUM CHLORIDE (CLORETO DE GUAR HIDROXIPROPILTRIMÔNIO)
PHENYLPROPANOL (FENILPROPANOL)
PENTYLENE GLYCOL (PENTILENOGLICOL)
LACTIC ACID (ÁCIDO LÁTICO)
1,2-HEXANEDIOL (1,2-HEXANODIOL)
PROPYLENE GLYCOL (PROPILENOGLICOL)
ALPHA-GLUCAN OLIGOSACCHARIDE (OLIGOSSACARÍDEO DE ALFA-GLUCANA)
C10-16 ALKETH-2 (C-10-16-ALQUETE-2)
SODIUM CHLORIDE (CLORETO DE SÓDIO)
SODIUM SULFATE (SULFATO DE SÓDIO)
SODIUM GLUCONATE (GLUCONATO DE SÓDIO)
BUTETH-3 (BUTETE-3)
SODIUM BENZOTRIAZOLYL BUTYLPHENOL SULFONATE (BENZOTRIAZOLIL BUTILFENOL SULFONATO DE SÓDIO)
SODIUM CITRATE (CITRATO DE SÓDIO)
BENZOIC ACID (ÁCIDO BENZÓICO)
TRIBUTYL CITRATE (CITRATO DE TRIBUTILA)
CITRIC ACID (ÁCIDO CÍTRICO)

PURPOSE

SOAP FOR INTIMATE USE

KEEP OUT OF REACH OF CHILDREN AND PETS. EXTERNAL USE.

KEEP OUT OF REACH OF CHILDREN

DOSAGE AND ADMINISTRATION

APPLY TO THE PREVIOUSLY MOISTENED EXTERNAL INTIMATE REGION. SPREAD UNTIL FOAMY. RINSE THOROUGHLY AFTER USE

QUESTIONS

MAIL : SUPPORT@MYSPRAY.GROUP OR CALL (305) 677-5030

INDICATIONS AND USAGE

APPLY TO THE PREVIOUSLY MOISTENED EXTERNAL INTIMATE REGION. SPREAD UNTIL FOAMY. RINSE THOROUGHLY AFTER USE

KEEP OUT OF REACH OF CHILDREN AND PETS. EXTERNAL USE.